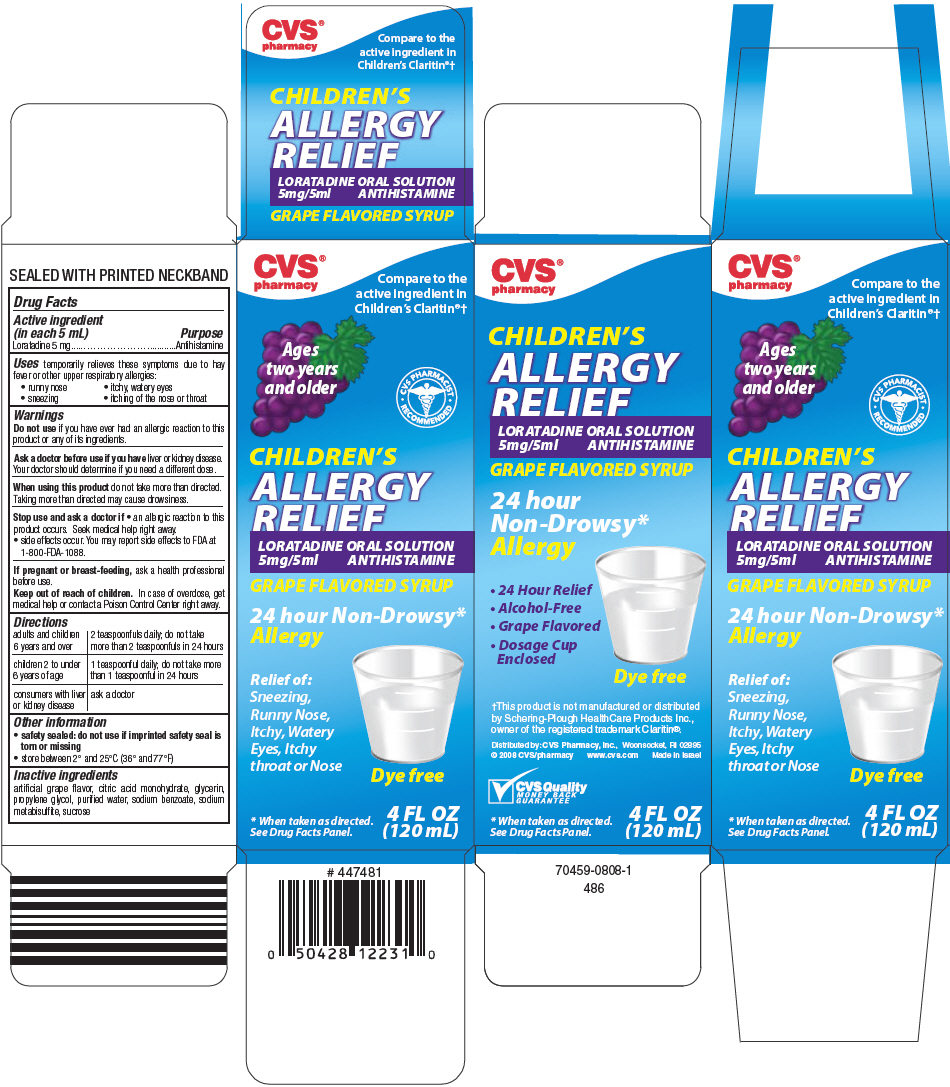 DRUG LABEL: Childrens Allergy Relief
NDC: 59779-446 | Form: SOLUTION
Manufacturer: CVS Pharmacy
Category: otc | Type: HUMAN OTC DRUG LABEL
Date: 20121127

ACTIVE INGREDIENTS: Loratadine 5 mg/5 mL
INACTIVE INGREDIENTS: Citric acid monohydrate; Glycerin; Propylene glycol; Water; Sodium Benzoate; Sodium metabisulfite; Sucrose

Children's Allergy Relief

Drug Facts

Active ingredient (in each 5 mL)

Loratadine 5 mg

Purpose

Antihistamine

Uses

temporarily relieves these symptoms due to hay fever or other upper respiratory allergies:

- runny nose
- itchy, watery eyes
- sneezing
- itching of the nose or throat

Warnings

Do not use if you have ever had an allergic reaction to this product or any of its ingredients.

Ask a doctor before use if you have liver or kidney disease. Your doctor should determine if you need a different dose.

When using this product do not take more than directed. Taking more than directed may cause drowsiness.

Stop use and ask a doctor if

- an allergic reaction to this product occurs. Seek medical help right away.
- side effects occur. You may report side effects to FDA at 1-800-FDA-1088.

PREGNANCY OR BREAST FEEDING

If pregnant or breast-feeding, ask a health professional before use.

Keep out of reach of children. In case of overdose, get medical help or contact a Poison Control Center right away.

Directions

adults and children 6 years and over | 2 teaspoonfuls daily; do not take more than 2 teaspoonfuls in 24 hours
children 2 to under 6 years of age | 1 teaspoonful daily; do not take more than 1 teaspoonful in 24 hours
consumers with liver or kidney disease | ask a doctor

Other information

- safety sealed: do not use if imprinted safety seal is torn or missing
- store between 2° and 25°C (36° and 77°F)

Inactive ingredients

artificial grape flavor, citric acid monohydrate, glycerin, propylene glycol, purified water, sodium benzoate, sodium metabisulfite, sucrose

Distributed by: CVS Pharmacy, Inc., Woonsocket, RI 02895

PRINCIPAL DISPLAY PANEL - 120 mL Bottle Carton

CVS®
pharmacy

Compare to the
active ingredient in
Children's Claritin®†

Ages
two years
and older

CVS PHARMACIST
RECOMMENDED

CHILDREN'S
ALLERGY
RELIEF

LORATADINE ORAL SOLUTION
5mg/5ml ANTIHISTAMINE

GRAPE FLAVORED SYRUP

24 hour Non-Drowsy*
Allergy

Relief of:
Sneezing,
Runny Nose,
Itchy, Watery
Eyes, Itchy
throat or Nose

Dye free

* When taken as directed.
See Drug Facts Panel.

4 FL OZ
(120 mL)